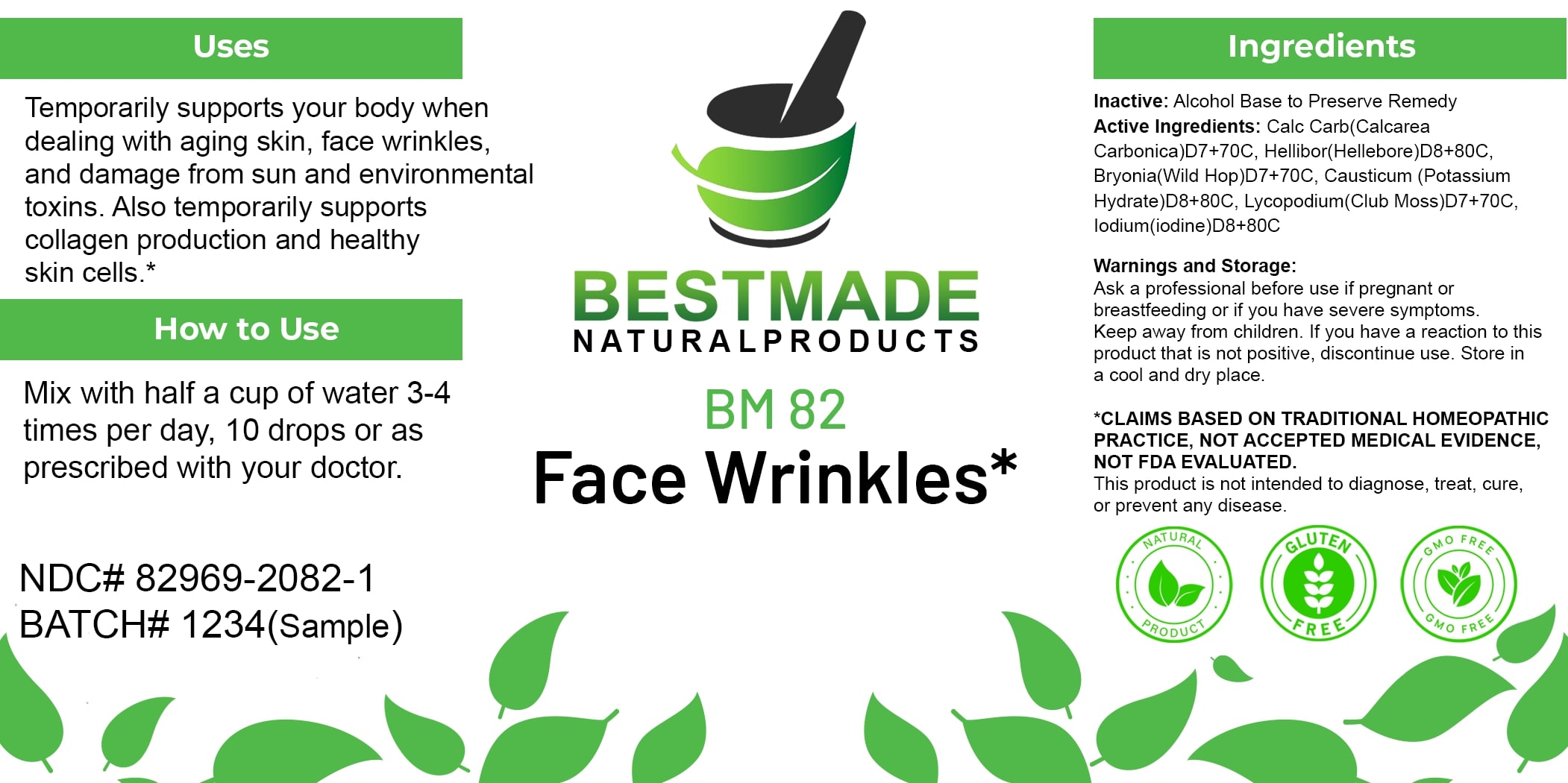 DRUG LABEL: Bestmade Natural Products BM82
NDC: 82969-2082 | Form: LIQUID
Manufacturer: Bestmade Natural Products
Category: homeopathic | Type: HUMAN OTC DRUG LABEL
Date: 20250131

ACTIVE INGREDIENTS: IODINE 30 [hp_C]/30 [hp_C]; LYCOPODIUM CLAVATUM SPORE 30 [hp_C]/30 [hp_C]; OYSTER SHELL CALCIUM CARBONATE, CRUDE 30 [hp_C]/30 [hp_C]; CAUSTICUM 30 [hp_C]/30 [hp_C]; HELLEBORUS NIGER ROOT 30 [hp_C]/30 [hp_C]; BRYONIA ALBA ROOT 30 [hp_C]/30 [hp_C]
INACTIVE INGREDIENTS: ALCOHOL 30 [hp_C]/30 [hp_C]

BM82

DOSAGE AND ADMINISTRATION

How to Use

Mix with half a cup of water 3-4 times per day, 10 drops or as prescribed with your doctor.

INACTIVE INGREDIENT

Ingredients

Inactive: Alcohol Base to Preserve Remedy

ACTIVE INGREDIENT

Active Ingredients: Calc Carb(Calcarea Carbonica)D7+70C, Hellibor(Hellebore)D8+80C, Bryonia(Wild Hop)D7+70C, Causticum (Potassium Hydrate)D8+80C, Lycopodium(Club Moss)D7+70C, Iodium(iodine)D8+80C

Uses

Temporarily supports your body when dealing with aging skin, face wrinkles, and damage from sun and environmental toxins. Also temporarily supports collagen production and healthy skin cells.*

*CLAIMS BASED ON TRADITIONAL HOMEOPATHIC PRACTICE, NOT ACCEPTED MEDICAL EVIDENCE, NOT FDA EVALUATED.

This product is not intended to diagnose, treat, cure, or prevent any disease.

Uses

Temporarily supports your body when dealing with aging skin, face wrinkles, and damage from sun and environmental toxins. Also temporarily supports collagen production and healthy skin cells.*

*CLAIMS BASED ON TRADITIONAL HOMEOPATHIC PRACTICE, NOT ACCEPTED MEDICAL EVIDENCE, NOT FDA EVALUATED.

This product is not intended to diagnose, treat, cure, or prevent any disease.

KEEP OUT OF REACH OF CHILDREN

Warnings and Storage:

Ask a professional before use if pregnant or breastfeeding or if you have severe symptoms. Keep away from children. If you have a reaction to this product that is not positive, discontinue use. Store in a cool and dry place.

Warnings and Storage:

Ask a professional before use if pregnant or breastfeeding or if you have severe symptoms. Keep away from children. If you have a reaction to this product that is not positive, discontinue use. Store in a cool and dry place.

*CLAIMS BASED ON TRADITIONAL HOMEOPATHIC PRACTICE, NOT ACCEPTED MEDICAL EVIDENCE, NOT FDA EVALUATED. This product is not intended to diagnose, treat, cure, or prevent any disease.

Entire package label